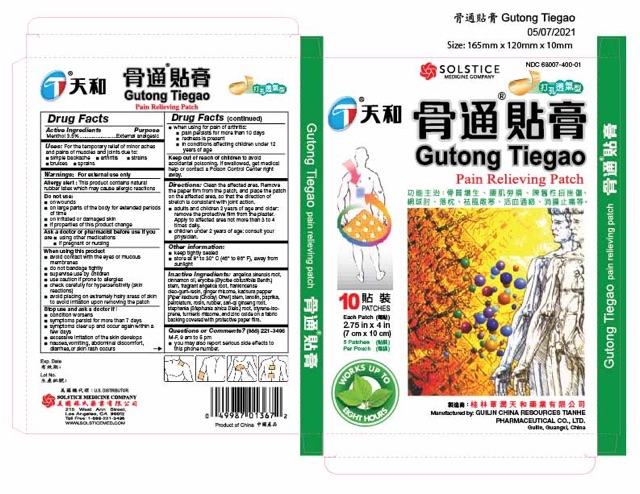 DRUG LABEL: Gutong Tiegao Pain Relieving
NDC: 68007-400 | Form: PLASTER
Manufacturer: GUILIN CHINA RESOURCES TIANHE PHARMACEUTICAL CO LTD
Category: otc | Type: HUMAN OTC DRUG LABEL
Date: 20250926

ACTIVE INGREDIENTS: MENTHOL 35 mg/1 1
INACTIVE INGREDIENTS: ANGELICA SINENSIS ROOT; CINNAMON OIL; ERYCIBE OBTUSIFOLIA STEM; ANGELICA DAHURICA ROOT; FRANKINCENSE; GINGER; PIPER KADSURA STEM; LANOLIN; PAPRIKA; PETROLATUM; ROSIN; NATURAL LATEX RUBBER; PANAX NOTOGINSENG ROOT; STEPHANIA SINICA WHOLE; STYRENE; ISOPRENE; TURMERIC; ZINC OXIDE

Drug Facts

Active Ingredients
Menthol 3.5%

Purpose
External Analgesic

Uses
For the temporary relief of minor aches and pains of muscles and joints due to:
■ simple backache ■ arthritis ■ strains ■ bruises ■ sprains

Warnings
For external use only

Allergy alert:This product contains natural rubber latex which may cause allergic reactions.

Do not use
■ on wounds
■ on large parts of the body for extended periods of time
■ on irritated or damaged skin
■ if properties of this product change

Ask a doctor or pharmacist before use if you have
■ using other medications
■ if pregnant or nursing

When using this product
■ avoid contact with the eyes or mucous membranes
■ do not bandage tightly
■ supervise use by children
■ use caution if prone to allergies
■ check carefully for hypersensitivity (skin reactions)
■ avoid placing on extremely hairy areas of skin to avoid irritation upon removing the patch

Stop use and ask a doctor if
■ condition worsens
■ symptoms persist for more than 7 days
■ symptoms clear up and occur again within a few days
■ excessive irritation of the skin develops
■ nausea, vomiting, abdominal discomfort, diarrhea, or skin rash occurs
■ when using for pain of arthritis:
■ pain persists for more than 10 days
■ redness is present
■ in conditions affecting children under 12 years of age

KEEP OUT OF REACH OF CHILDREN

Keep out of reach of childrento avoid accidental poisoning. If swallowed, get medical help or contact a Poison Control Center right away.

Directions
Clean the affected area. Remove the paper film from the patch, and place the patch on the affected area, so that the direction of stretch is consistent with joint action.
■ adults and children 2 years of age and older: remove the protective film from the plaster. Apply to affected area not more than 3 to 4 times daily.
■ children under 2 years of age: consult your physician.

Other information
■ keep tightly sealed
■ store at 8 to 30 C (46 to 86 F), away from sunlight

INACTIVE INGREDIENT

Inactive ingredientsangelica sinensis root, cinnamon oil, erycibe (Erycibe obtusifolia Benth.) stem, fragrant angelica root, frankincense oleo-gum-resin, ginger rhizome, kadsura pepper [Piper kadsura (Choisy) Ohwi] stem, lanolin, paprika, petrolatum, rosin, rubber, san-qi ginseng root, stephania (Stephania sinica Diels.) root, styrene-isoprene, turmeric rhizome, and zinc oxide on a fabric backing covered with protective paper film.

Questions or comments?
(888) 221-3496M-F 9 am to 5 pm
■ you may also report serious side effects to this phone number

PACKAGE LABEL

Gutong Tiegao Pain Relieving Plaster

NDC 68007-400-01

10 Patches
Each Patch 2.75 in x 4 in (7 cm x 10 cm)
5 Patches per Pouch